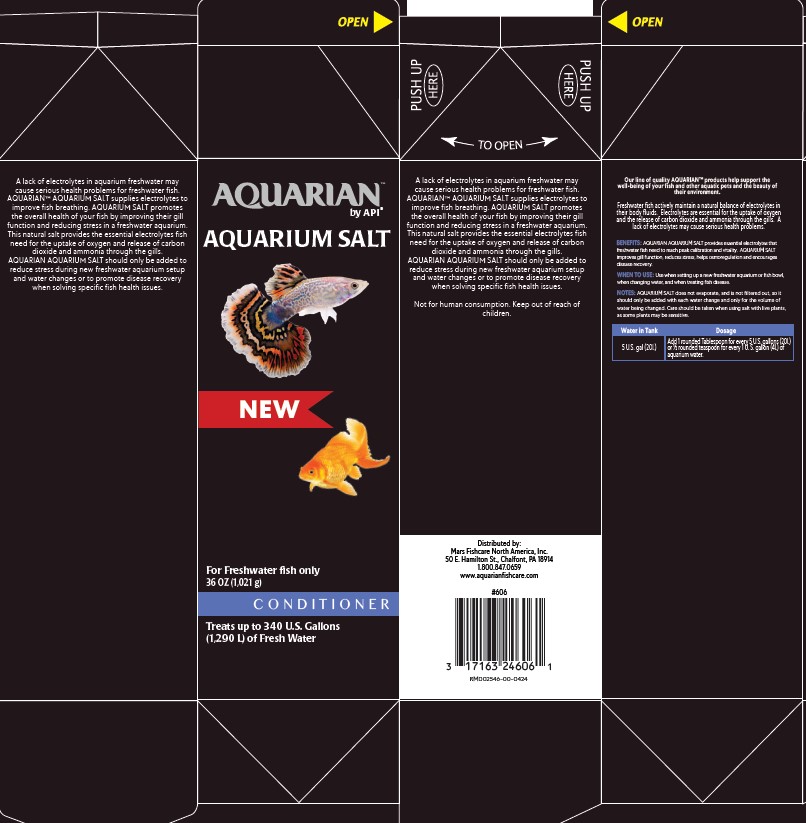 DRUG LABEL: AQUARIAN AQUARIUM SALT
NDC: 17163-241 | Form: GRANULE, FOR SOLUTION
Manufacturer: MARS FISHCARE NORTH AMERICA, INC.
Category: animal | Type: OTC ANIMAL DRUG LABEL
Date: 20240625

ACTIVE INGREDIENTS: SODIUM CHLORIDE 100 g/100 g

Drug Label

DESCRIPTION

A lack of electrolytes in aquarium freshwater may cause serious health problems for freshwater fish. AQUARIAN™ AQUARIUM SALT supplies electrolytes to improve fish breathing. AQUARIUM SALT promotes the overall health of your fish by improving their gill function and reducing stress in a freshwater aquarium. This natural salt provides the esssential electrolytes fish need for the update of oxygen and release of carbon dioxide and ammonia through the gills.

AQUARIAN AQUARIUM SALT should only be added to reduce stress during new freshwater aquarium setup andand water changes or to promote disease recovery when solving specific fish health issue.

Not for human consumption. Keep out of reach of children.

Our line of quality AQUARIAN™ products help support the well-being of your fishand other aquatic pets and the beauty of their environment.

Freshwater fish actively maintain a natural balance of electrolyetes in their body fluids. Electrolytes are essential for the uptake of oxygen and the release of carbon dioxide and ammonia through the gills. A lack of electrolytes may cause serious health problems.

BENEFITS: AQUARIAN AQUARIUM SALT provides essential electrolytes that freshwater fish need to reach peak calibration and vitality. AQUARIUM SALT improves gill function, reduces stress, helps osmoregulation and emcourages disease recovery.

INDICATIONS AND USAGE

WHEN TO USE: Use when setting up a freshwater aquarium or fish bowl, when changing water and when treating fish disease.

DOSAGE AND ADMINISTRATION

Water in Tank

5 U.S gal (20L)

Dosage

Add 1 rounded Tablespoon for every 5 U.S. gallons (20 L) or 1/2 rounded teaspoon for every 1 U.S. (4 L) of aquarium water.

USER SAFETY WARNINGS

NOTES:

AQUARIUM SALT does not evaporate and is not filtered out, so it should only be added with each water change and only for the volume of water being changed. Care should be taken when using salt with live plants, as some plants may be sensitive.

PACKAGE LABEL

AQUARIAN™

by API®

AQUARIUM SALT

NEW

For Freshwater fish only

36 OZ (1,021g)

CONDITIONER

Treats up to 340 U.S. Gallons

(1,290 L) of Fresh Water